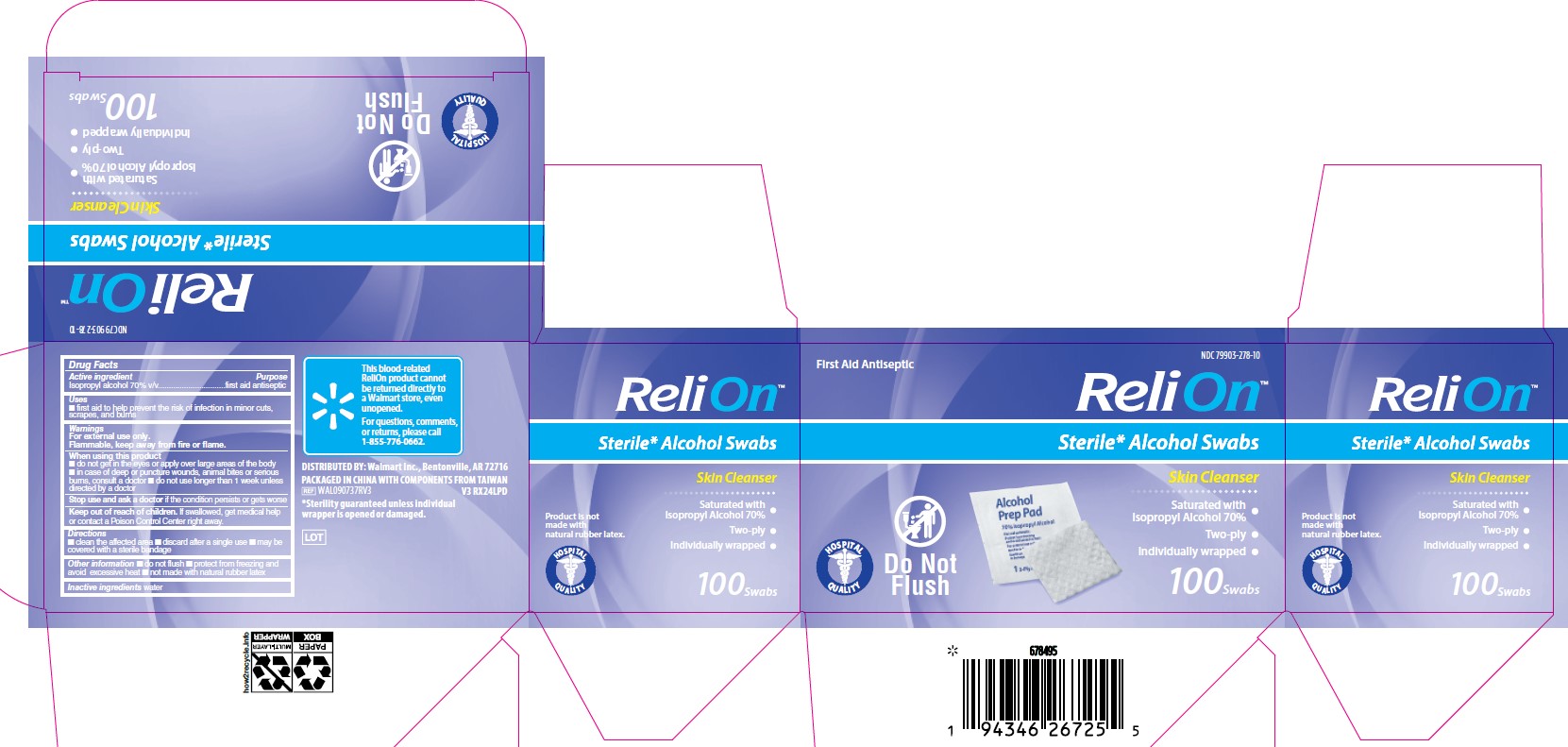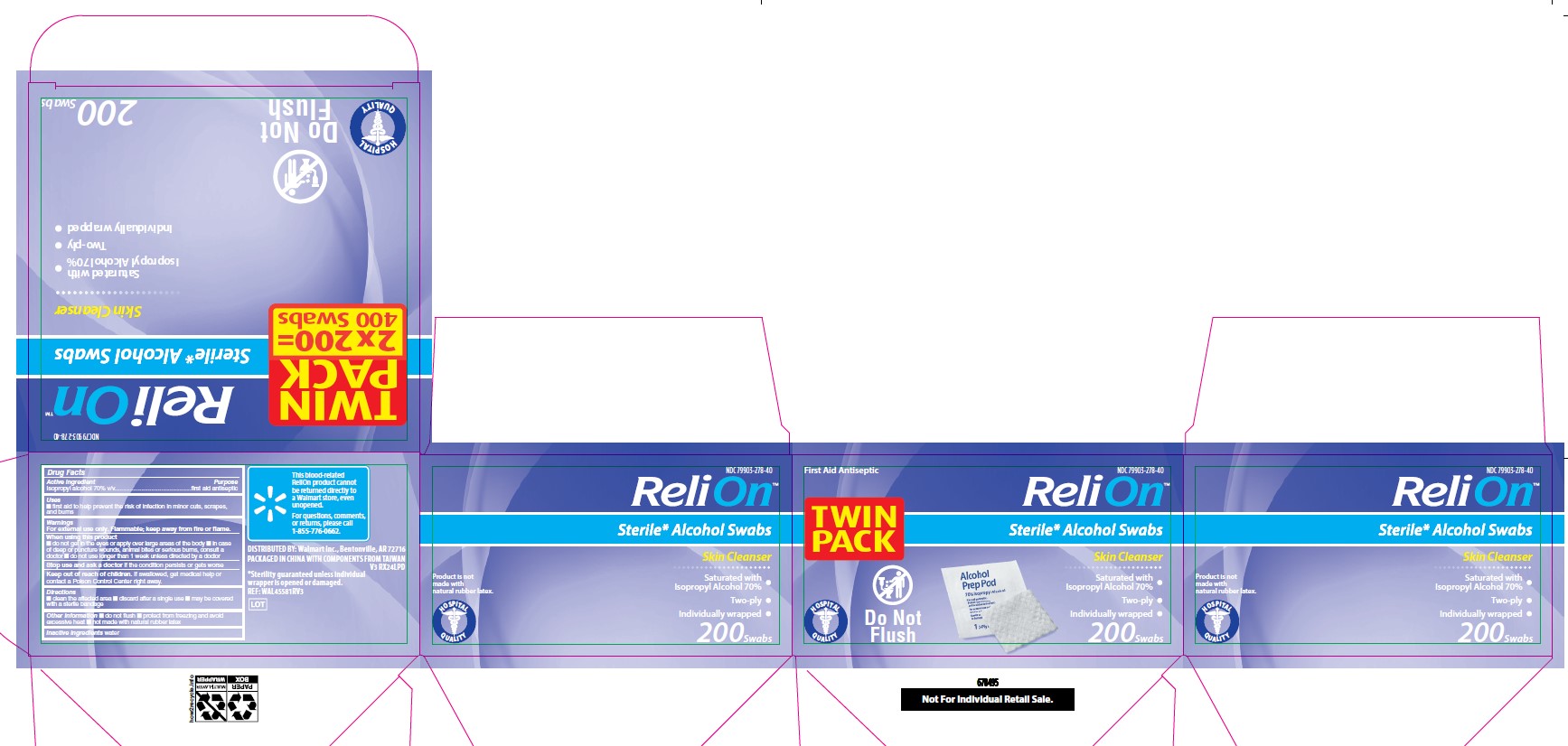 DRUG LABEL: Walmart
NDC: 79903-278 | Form: SWAB
Manufacturer: Walmart Inc.
Category: otc | Type: HUMAN OTC DRUG LABEL
Date: 20260129

ACTIVE INGREDIENTS: ISOPROPYL ALCOHOL 70 mL/100 mL
INACTIVE INGREDIENTS: WATER

79903-278 Walmart Sterile Alcohol Swabs

Active Ingredient

Isopropyl alcohol 70% v/v

Purpose

first aid antiseptic

Uses

- first aid to help prevent the risk of infection in minor cuts, scrapes, and burns

Warnings

For external use only.

Flammable, keep away from fire or flame.

When using this product

- do not get in the eyes or apply over large areas of the body
- in case of deep or puncture wounds, animal bites or serious burns, consult a doctor
- do not use longer than 1 week unless directed by a doctor

Stop use and ask a doctor

if the condition persists or gets worse

Keep out of reach of children

If swallowed, get medical help or contact a Poison Control Center right away.

Directions

- clean the affected area
- discard after a single use
- may be covered with a sterile bandage

Other information

- do not flush
- protect from freezing and avoid excessive heat
- not made with natural rubber latex

Inactive ingredients

water

Other information

This blood-related ReliOn product cannot be returned directly to a Walmart store, even unopened.

For questions, comments, or returns, please call 1-855-776-0662

DISTRIBUTED BY: Walmart Inc., Bentonville, AR 72716

PACKAGED IN CHINA WITH COMPONENTS FROM TAIWAN

*Sterility guaranteed unless individual wrapper is opened or damaged.